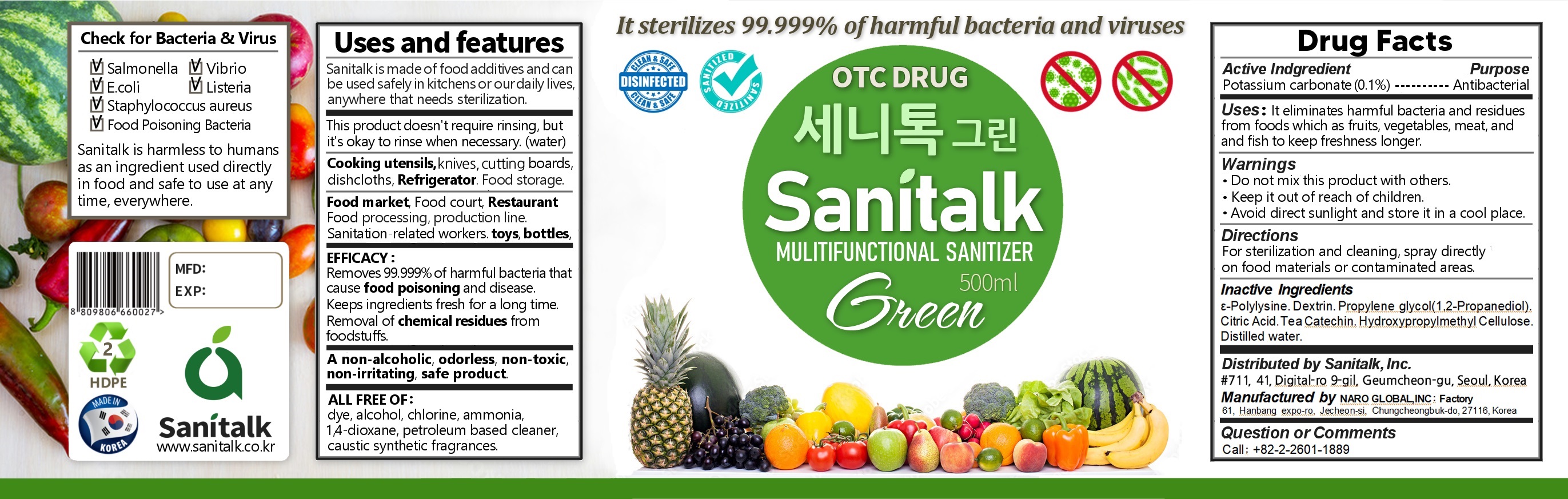 DRUG LABEL: SANITALK GREEN - FRUIT ,VEGETABLE
NDC: 82486-0002 | Form: LIQUID
Manufacturer: Sanitalk Inc
Category: otc | Type: HUMAN OTC DRUG LABEL
Date: 20220114

ACTIVE INGREDIENTS: POTASSIUM CARBONATE 0.1 g/100 mL
INACTIVE INGREDIENTS: CITRIC ACID MONOHYDRATE; WATER

ACTIVE INGREDIENT

potassium carbonate

INACTIVE INGREDIENT

ε-Polylysine.Dextrin.1,2-Propanediol.Citric Acid.Tea Catechin. Hydroxypropylmethyl Cellulose.Distilled water.

PURPOSE

Helps to kill bacteria and germs on foods, and remove harmful residues on meats and vegetables.

keep out of reach of the children

INDICATIONS AND USAGE

For hygienic disinfection, this product can be used directly to the surface. Also, you can dilute one part product with two parts water

WARNINGS

For external use only.

When using this product

Avoid contact with eyes. Discontinue use if signs of irritation or rashes appear.

Keep out of reach of children.

Store at room temperature.

DOSAGE AND ADMINISTRATION

for external use only